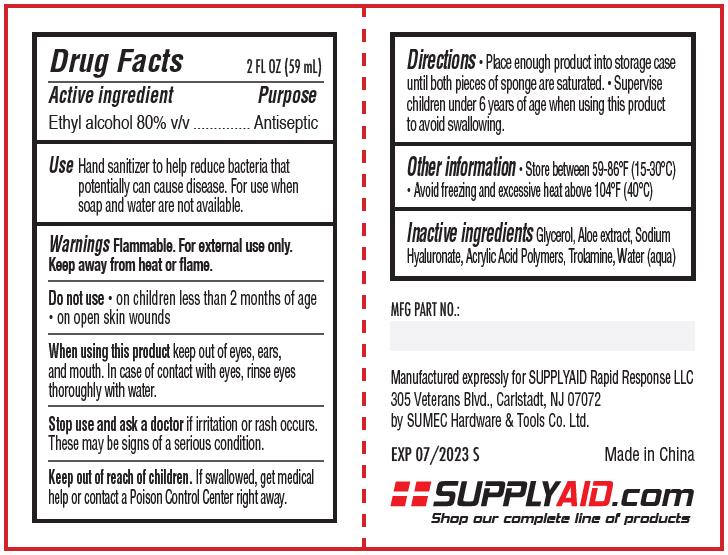 DRUG LABEL: RRS-KEY1
NDC: 74035-1061 | Form: GEL
Manufacturer: SUMEC Hardware & Tools Co., Ltd.
Category: otc | Type: HUMAN OTC DRUG LABEL
Date: 20200715

ACTIVE INGREDIENTS: ALCOHOL 47.2 mL/59 mL
INACTIVE INGREDIENTS: ALOE VERA LEAF; TROLAMINE; WATER; GLYCERIN; HYALURONATE SODIUM; DENATONIUM BENZOATE ANHYDROUS; CARBOMER INTERPOLYMER TYPE A (ALLYL SUCROSE CROSSLINKED)

SUMEC, Hand Sanitizer, Gel, 80% Ethyl alcohol, 59mL

Active Ingredient(s)

Ethyl alcohol 80% v/v. Purpose: Antiseptic

Purpose

Antiseptic, Hand Sanitizer

Use

Hand Sanitizer to help reduce bacteria that potentially can cause disease. For use when soap and water are not available.

Warnings

Flammable. For external use only. Keep away from heat or flame.

Do not use

- on children less than 2 months of age
- on open skin wounds

When using this product keep out of eyes, ears, and mouth.

In case of contact with eyes, rinse eyes thoroughly with water.

Stop use and ask a doctor if irritation or rash occurs. These may be signs of a serious condition.

Keep out of reach of children. If swallowed, get medical help or contact a Poison Control Center right away.

Directions

- Place enough product into storage case until both pieces of sponge are saturated.
- Supervise children under 6 years of age when using this product to avoid swallowing.

Other information

- Store between 59-86℉ (15-30℃)
- Avoid freezing and excessive heat above 104℉ (40℃)

Inactive ingredients

Glycerol, Aloe extract, Sodium Hyaluronate, Acrylic Acid Polymers, Trolamine, Denatonium, Water (aqua)